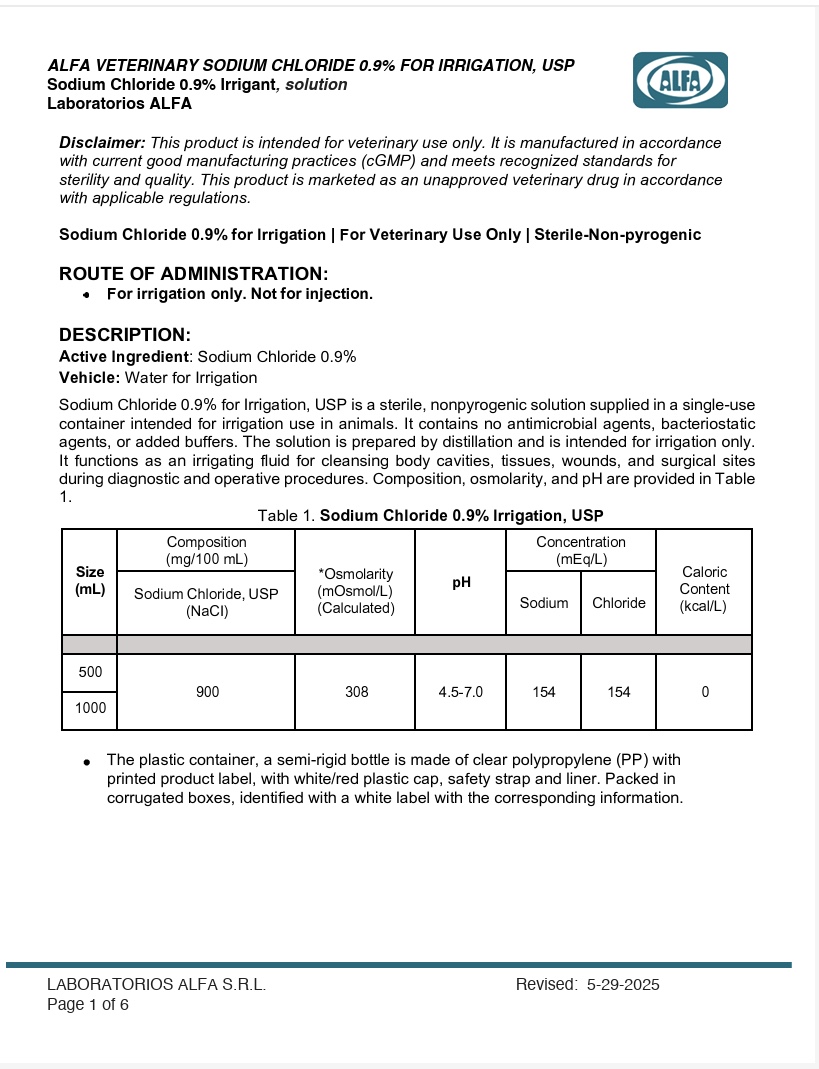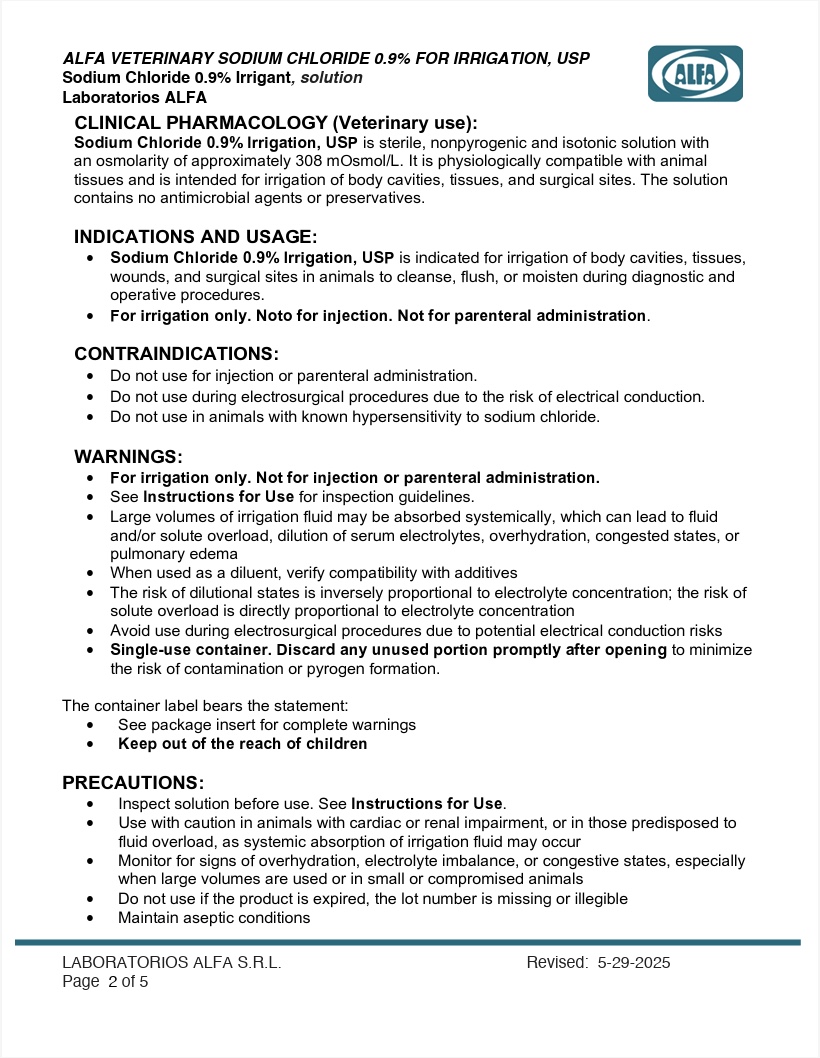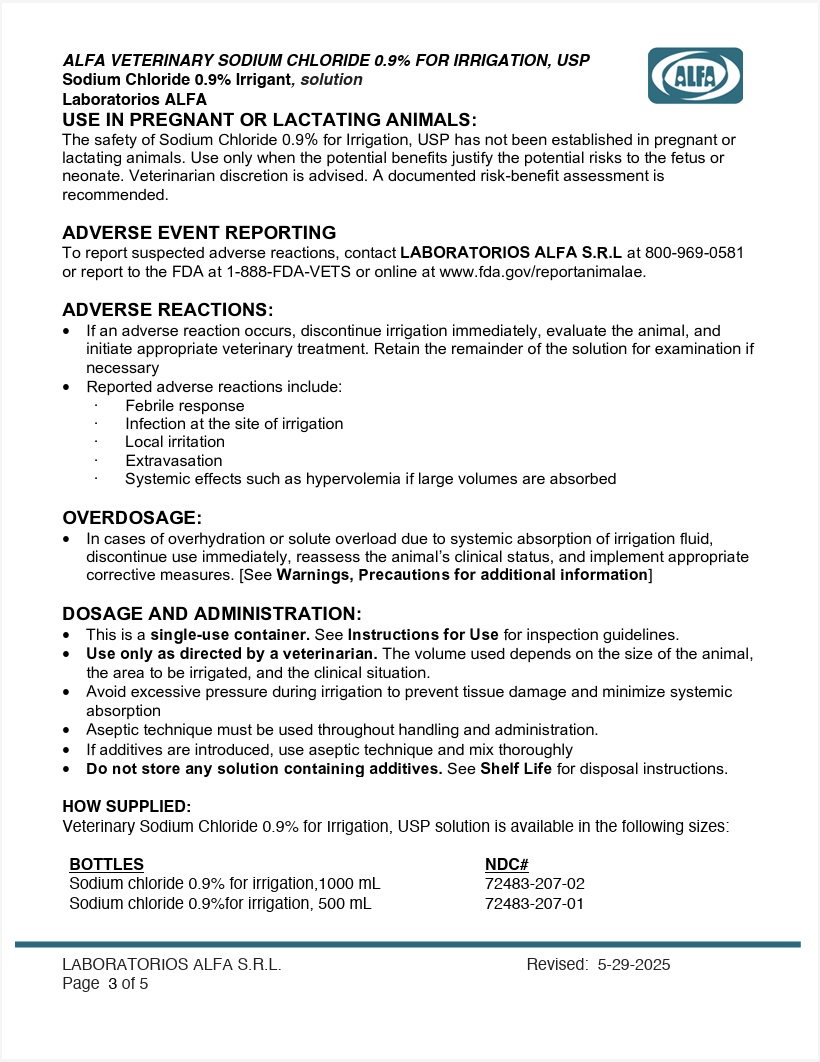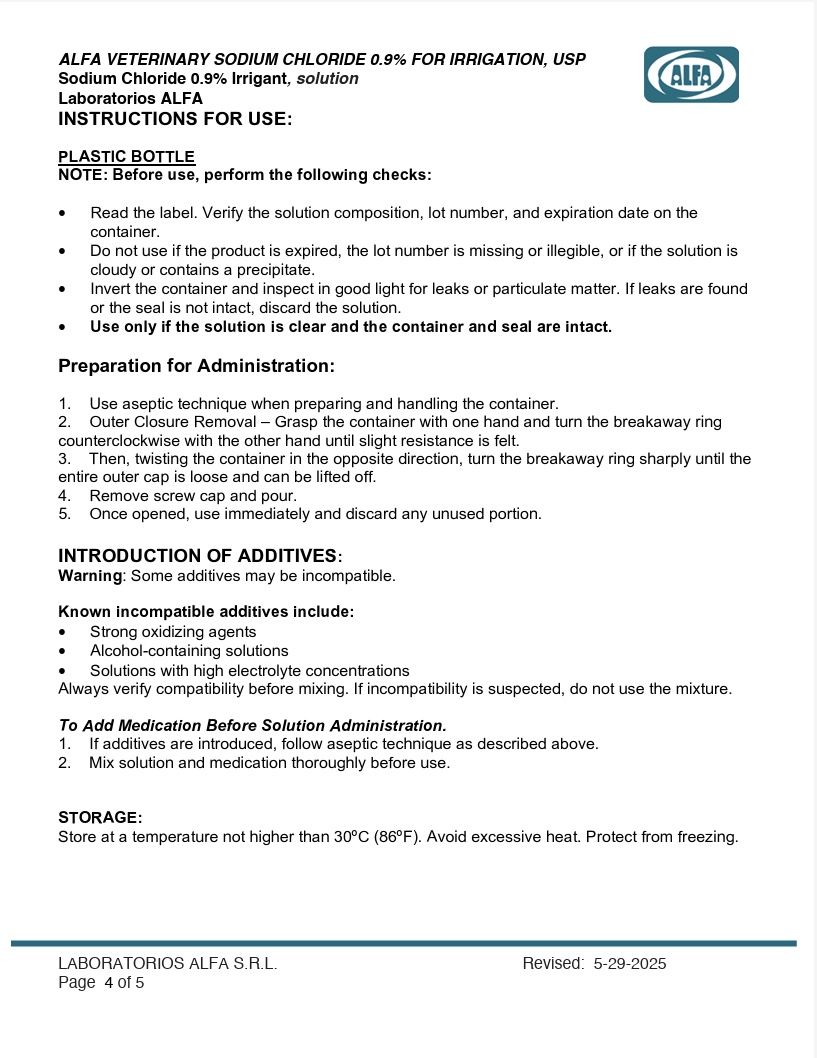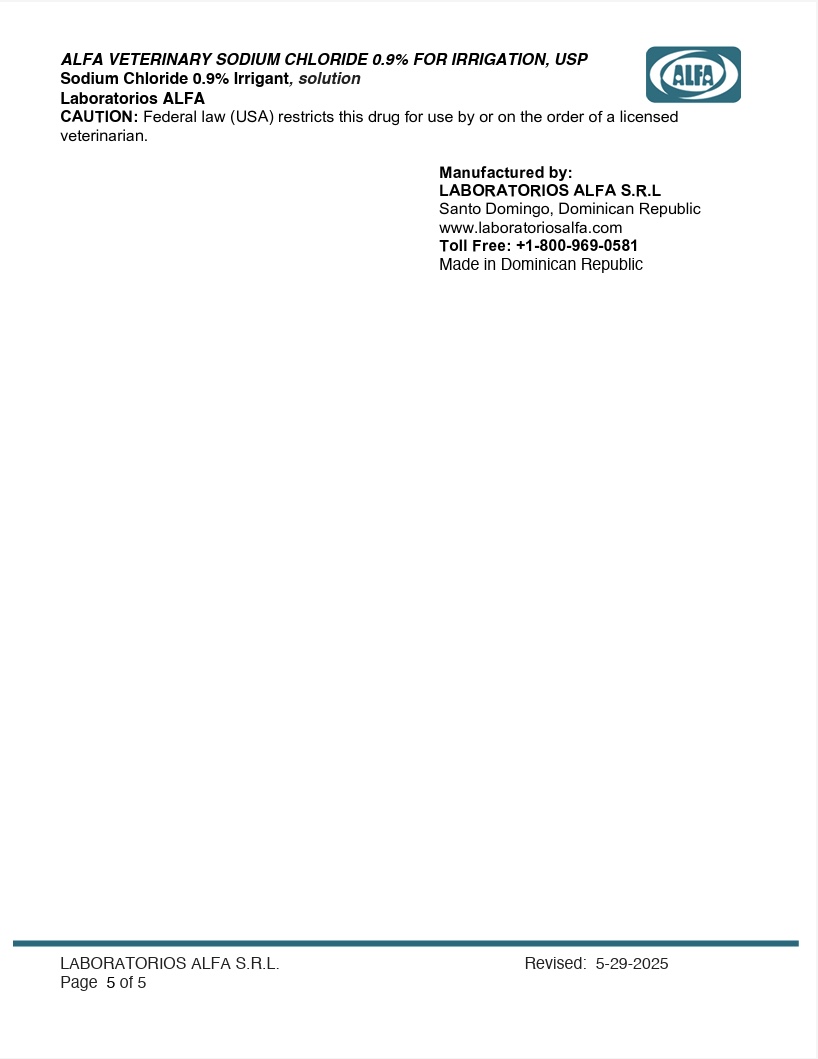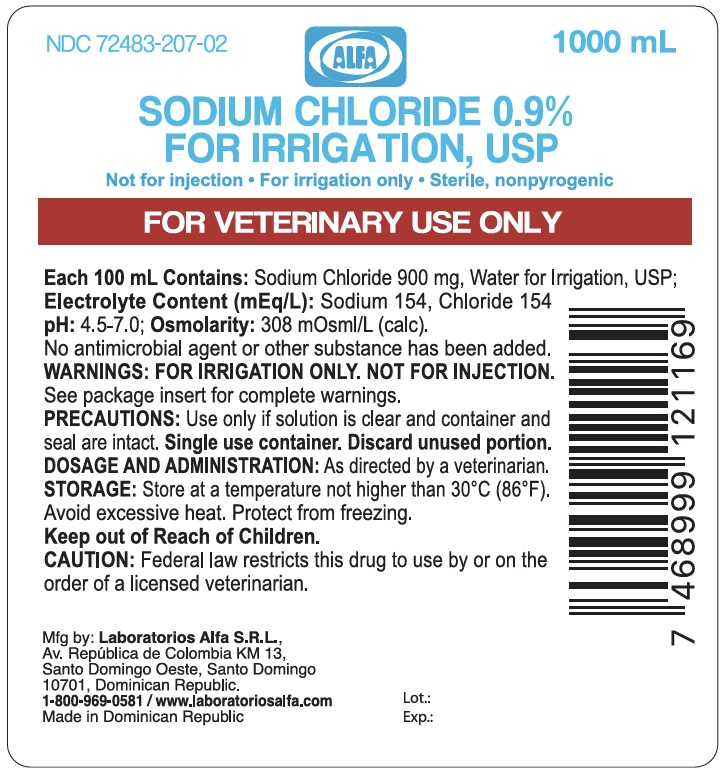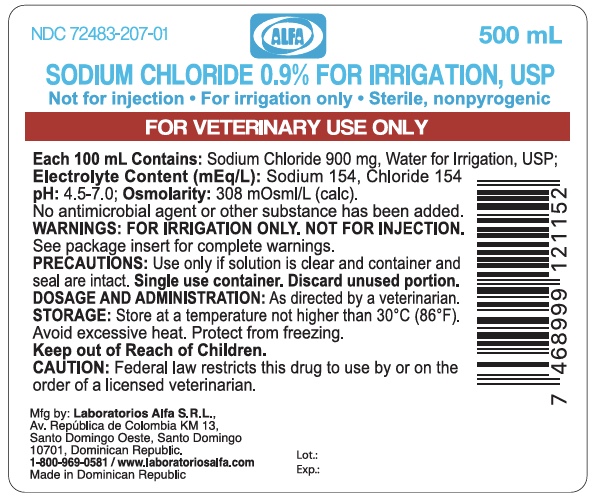 DRUG LABEL: Alfa Veterinary 0.9% Sodium Chloride
NDC: 72483-207 | Form: IRRIGANT
Manufacturer: Laboratorios Alfa SRL
Category: animal | Type: PRESCRIPTION ANIMAL DRUG LABEL
Date: 20260114

ACTIVE INGREDIENTS: SODIUM CHLORIDE 900 mg/100 mL
INACTIVE INGREDIENTS: Water

DESCRIPTION:

Disclaimer: This product is intended for veterinary use only. It is manufactured in accordance with current good manufacturing practices (cGMP) and meets recognized standards for sterility and quality. This product is marketed as an unapproved veterinary drug in accordance with applicable regulations.

Sodium Chloride 0.9% for Irrigation | For Veterinary Use Only | Sterile-Non-pyrogenic

ROUTE OF ADMINISTRATION: For irrigation only

DESCRIPTION:

Active Ingredient: Sodium Chloride 0.9%
Vehicle: Water for Irrigation
Sodium Chloride 0.9% for Irrigation, USP is a sterile, nonpyrogenic solution supplied in a single-use container intended for irrigation use in animals. It contains no antimicrobial agents, bacteriostatic agents, or added buffers. The solution is prepared by distillation and is intended for irrigation only. It functions as an irrigating fluid for cleansing body cavities, tissues, wounds, and surgical sites during diagnostic and operative procedures. Composition, osmolarity, and pH are provided in Table 1.

Table 1.Sodium Chloride for Irrigation 0.9% Irrigation, USP

Size (mL) | Composition (mg/100 mL) | *Osmolarity (mOsmol/L)(Calculated) | pH | Concentration (mEq/L) |  | Caloric Content (kcal/L)
Size (mL) | Sdoium Chloride, USP (Nacl) | *Osmolarity (mOsmol/L)(Calculated) | pH | Sodium | Chloride | Caloric Content (kcal/L)
500 | 900 | 308 | 4.5-7.0 | 154 | 154 | 0
1000 | 900 | 308 | 4.5-7.0 | 154 | 154 | 0

The plastic container, a semi-rigid bottle is made of clear polypropylene (PP) with printed product label, with white/red plastic cap, safety strap and liner. Packed in corrugated boxes, identified with a white label with the corresponding information.

OTHER SAFETY INFORMATION

CAUTION: Federal law (USA) restricts this drug to use by or on the order of a licensed veterinarian.

CLINICAL PHARMACOLOGY (Veterinary Use):

Sodium Chloride 0.9% Irrigation, USP is sterile, nonpyrogenic and isotonic solution with an osmolarity of approximately 308 mOsmol/L. It is physiologically compatible with animal tissues and is intended for irrigation of body cavities, tissues, and surgical sites. The solution contains no antimicrobial agents or preservatives.

INDICATIONS AND USAGE:

• Sodium Chloride 0.9% Irrigation, USP is indicated for irrigation of body cavities, tissues, wounds, and surgical sites in animals to cleanse, flush, or moisten during diagnostic and operative procedures.
• For irrigation only. Noto for injection. Not for parenteral administration.

CONTRAINDICATIONS:

Do not use for injection or parenteral administration. Do not use during electrosurgical procedures due to the risk of electrical conduction. • Do not use in animals with known hypersensitivity to sodium chloride.

WARNINGS:

• For irrigation only. Not for injection or parenteral administration.
• See Instructions for Use for inspection guidelines.
• Large volumes of irrigation fluid may be absorbed systemically, which can lead to fluid and/or solute overload, dilution of serum electrolytes, overhydration, congested states, or pulmonary edema
• When used as a diluent, verify compatibility with additives
• The risk of dilutional states is inversely proportional to electrolyte concentration; the risk of solute overload is directly proportional to electrolyte concentration
• Avoid use during electrosurgical procedures due to potential electrical conduction risks
• Single-use container. Discard any unused portion promptly after opening to minimize the risk of contamination or pyrogen formation.

The container label bears the statement:
• See package insert for complete warnings
• Keep out of the reach of children

PRECAUTIONS:

• Inspect solution before use. See Instructions for Use.
• Use with caution in animals with cardiac or renal impairment, or in those predisposed to fluid overload, as systemic absorption of irrigation fluid may occur
• Monitor for signs of overhydration, electrolyte imbalance, or congestive states, especially when large volumes are used or in small or compromised animals
• Do not use if the product is expired, the lot number is missing or illegible
• Maintain aseptic conditions

USE IN PREGNANT OR LACTATING ANIMALS:

The safety of Sodium Chloride 0.9% for Irrigation, USP has not been established in pregnant or lactating animals. Use only when the potential benefits justify the potential risks to the fetus or neonate. Veterinarian discretion is advised. A documented risk-benefit assessment is recommended.

ADVERSE EVENT REPORTING
To report suspected adverse reactions, contact Vedco Inc. at (888) 708-3326 or report to the FDA at 1-888-FDA-VETS or online at www.fda.gov/reportanimalae.

ADVERSE REACTIONS:

If an adverse reaction occurs, discontinue irrigation immediately, evaluate the animal, and initiate appropriate veterinary treatment. Retain the remainder of the solution for examination if necessary. • Reported adverse reactions include: · Febrile response, · Infection at the site of irrigation, · Local irritation, · Extravasation, · Systemic effects such as hypervolemia if large volumes are absorbed

OVERDOSAGE:

• In cases of overhydration or solute overload due to systemic absorption of irrigation fluid, discontinue use immediately, reassess the animal’s clinical status, and implement appropriate corrective measures. [See Warnings, Precautions for additional information]

DOSAGE AND ADMINISTRATION:

• This is a single-use container. See Instructions for Use for inspection guidelines.
• Use only as directed by a veterinarian. The volume used depends on the size of the animal, the area to be irrigated, and the clinical situation.
• Avoid excessive pressure during irrigation to prevent tissue damage and minimize systemic absorption
• Aseptic technique must be used throughout handling and administration.
• If additives are introduced, use aseptic technique and mix thoroughly
• Do not store any solution containing additives. See Shelf Life for disposal instructions.

HOW SUPPLIED:

Veterinary Sodium Chloride 0.9% for Irrigation, USP solution is available in the following sizes:

BOTTLES NDC#

Sodium chloride 0.9% for Irrigation, 500 mL NDC 72483-207-01

Sodium chloride 0.9% for Irrigation,1000 mL NDC 72483-207-02

INSTRUCTIONS FOR USE:

PLASTIC BOTTLE
NOTE: Before use, perform the following checks:

• Read the label. Verify the solution composition, lot number, and expiration date on the container.
• Do not use if the product is expired, the lot number is missing or illegible, or if the solution is cloudy or contains a precipitate.
• Invert the container and inspect in good light for leaks or particulate matter. If leaks are found or the seal is not intact, discard the solution.
• Use only if the solution is clear and the container and seal are intact.

Preparation for Administration:

1. Use aseptic technique when preparing and handling the container.
2. Outer Closure Removal – Grasp the container with one hand and turn the breakaway ring counterclockwise with the other hand until slight resistance is felt.
3. Then, twisting the container in the opposite direction, turn the breakaway ring sharply until the entire outer cap is loose and can be lifted off.
4. Remove screw cap and pour.
5. Once opened, use immediately and discard any unused portion.

INTRODUCTION OF ADDITIVES:
Warning: Some additives may be incompatible.

Known incompatible additives include:
• Strong oxidizing agents
• Alcohol-containing solutions
• Solutions with high electrolyte concentrations

Always verify compatibility before mixing. If incompatibility is suspected, do not use the mixture.

To Add Medication Before Solution Administration.
1. If additives are introduced, follow aseptic technique as described above.
2. Mix solution and medication thoroughly before use.

STORAGE:

Store at a temperature not higher than 30ºC (86ºF). Avoid excessive heat. Protect from freezing.

CAUTION: Federal law restricts this drug (USA) for use by or on the order of a licensed veterinarian.

Manufactured by:
LABORATORIOS ALFA S.R.L
Santo Domingo, Dominican Republic
www.laboratoriosalfa.com
Toll Free: +1-800-969-0581
Made in Dominican Republic

PACKAGE INSERT

For Animal Use Only

0.9% SODIUM CHLORIDE 0.9%, FOR IRRIGATION USP

For Veterinary Use Only

Sodium chloride 0.9% for Irrigation, 500 mL NDC 72483-207-01

Sodium chloride 0.9% for Irrigation,1000 mL NDC 72483-207-02